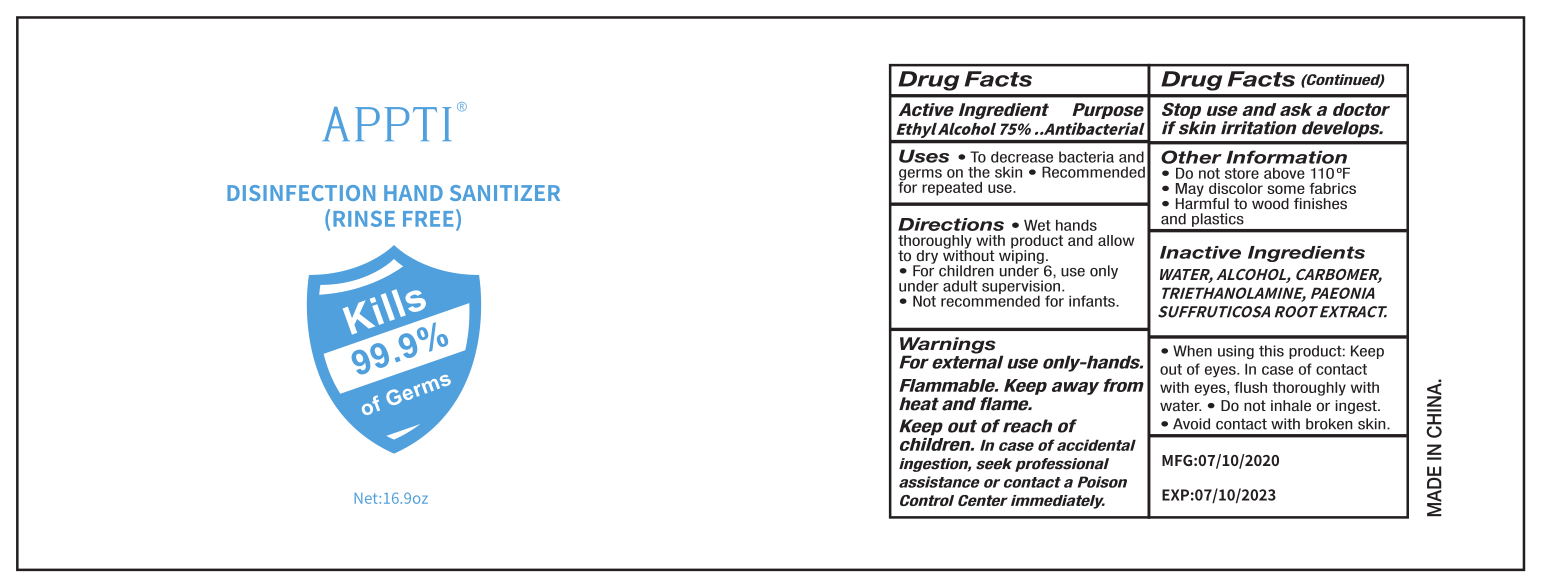 DRUG LABEL: Hand Sanitizer
NDC: 81309-002 | Form: GEL
Manufacturer: LYW BIOTECH CO LIMITED GUANGZHOU
Category: otc | Type: HUMAN OTC DRUG LABEL
Date: 20210113

ACTIVE INGREDIENTS: ALCOHOL 75 mL/100 mL
INACTIVE INGREDIENTS: ALOE ARBORESCENS LEAF 0.01 mL/100 mL; GLYCERIN 0.01 mL/100 mL; TROLAMINE 0.4 mL/100 mL; TOCOPHERYL NICOTINATE 0.01 mL/100 mL; WATER 24.17 mL/100 mL; CARBOMER 940 0.4 mL/100 mL

Hand Sanitizer